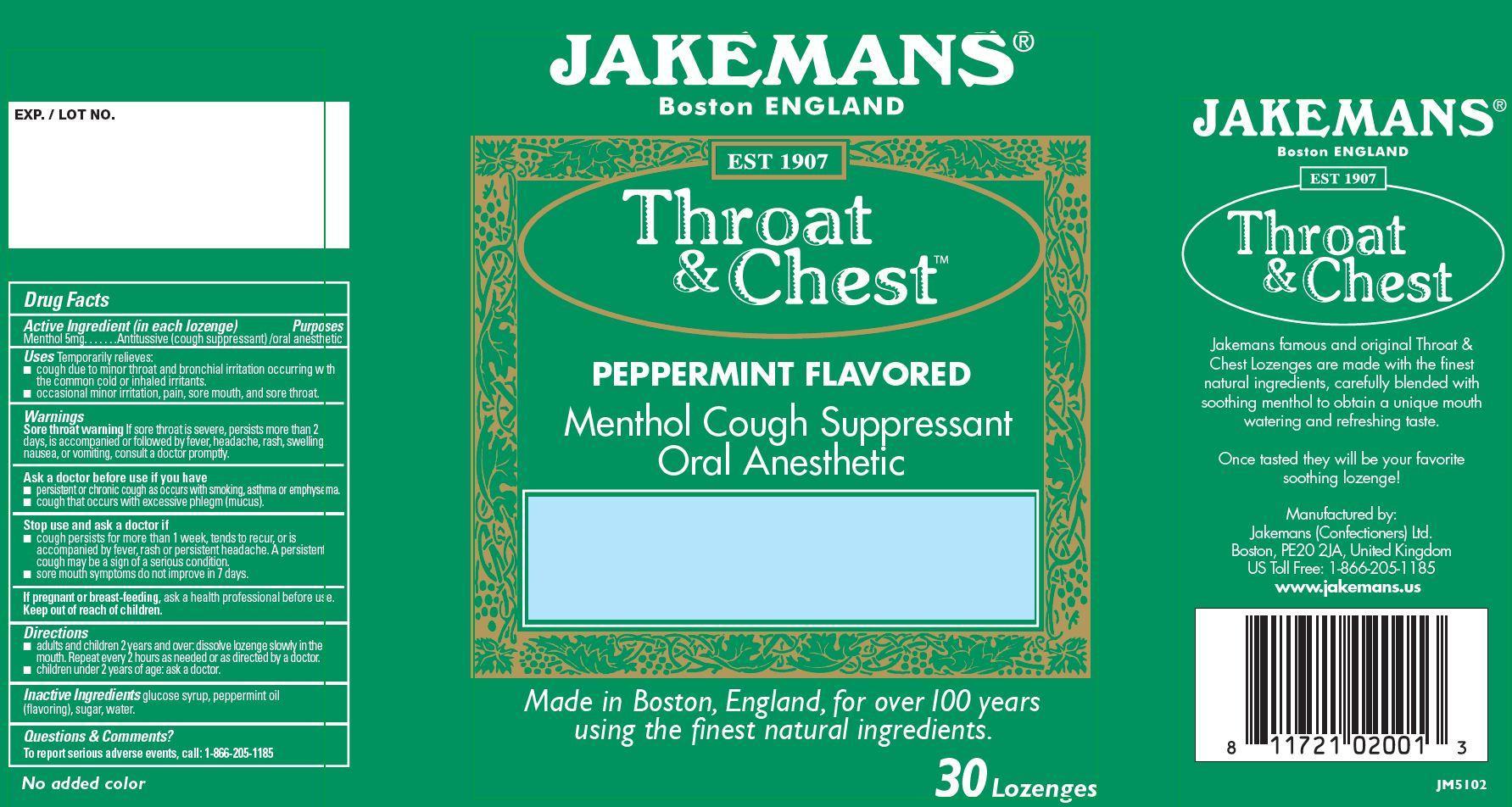 DRUG LABEL: Jakemans Throat and Chest Peppermint
NDC: 42637-824 | Form: LOZENGE
Manufacturer: Jakemans (Confectioners) Ltd.
Category: otc | Type: HUMAN OTC DRUG LABEL
Date: 20231101

ACTIVE INGREDIENTS: MENTHOL 5 mg/1 1
INACTIVE INGREDIENTS: CORN SYRUP; SUCROSE; WATER; PEPPERMINT OIL

Jakemans Throat and Chest Peppermint

Active Ingredient (in each lozenge) Purpose

Menthol 5mg ........ Antitussive (cough suppressant)/oral anesthetic

PURPOSE

JAKEMANS® Boston ENGLAND Est 1907

Throat & Chest™ Peppermint Flavored Menthol Cough Suppressant Oral Anesthetic

Made in Boston, England, for over 100 years using the finest natural ingredients.

30 Lozenges

Jakemans famous and original Throat & Chest Lozenges are made with the finest natural ingredients, carefully blended with soothing menthol to obtain a unique mouth watering and refreshing taste. Once tasted they will be your favorite soothing lozenge!

Manufactured by:

Jakemans (Confectioners) Ltd.

Boston PE20 2JA, United Kingdom

US Toll Free: 1-866-205-1185

www.jakemans.us

Keep out of reach of children.

Uses

Temporarily relieves

- cough due to minor throat and bronchial irritation occurring with the common cold or inhaled irritants.
- occasional minor irritation, pain, sore mouth, and sore throat.

Warnings

Sore throat warning If sore throat is severe, persists more than 2 days, is accompanied or followed by fever ,headache, rash, swelling, nausea, or vomiting, consult a doctor promptly.

Ask a doctor before use if you have

persistent or chronic cough as occurs with smoking, asthma or emphysema
cough that occurs with excessive phlegm (mucus).

Stop use and ask a doctor if

cough persists for more than 1 week, tends to recur, or is accompanied by fever, rash, or persistent headache. A persistent cough may be a sign of a serious condition.
sore mouth symptoms do not improve in 7 days.

If pregnant or breast-feeding, ask a health professional before use.

Directions

- adults and children 2 years and over: dissolve lozenge slowly in the mouth. Repeat every 2 hours as needed or as directed by a doctor.
- children under 2 years of age: ask a doctor.

INACTIVE INGREDIENT

Inactive Ingredients glucose syrup, peppermint oil (flavoring), sugar, water.

OTHER SAFETY INFORMATION

Questions & Comments?

To report serious adverse events, call: 1-866-205-1185

No added color